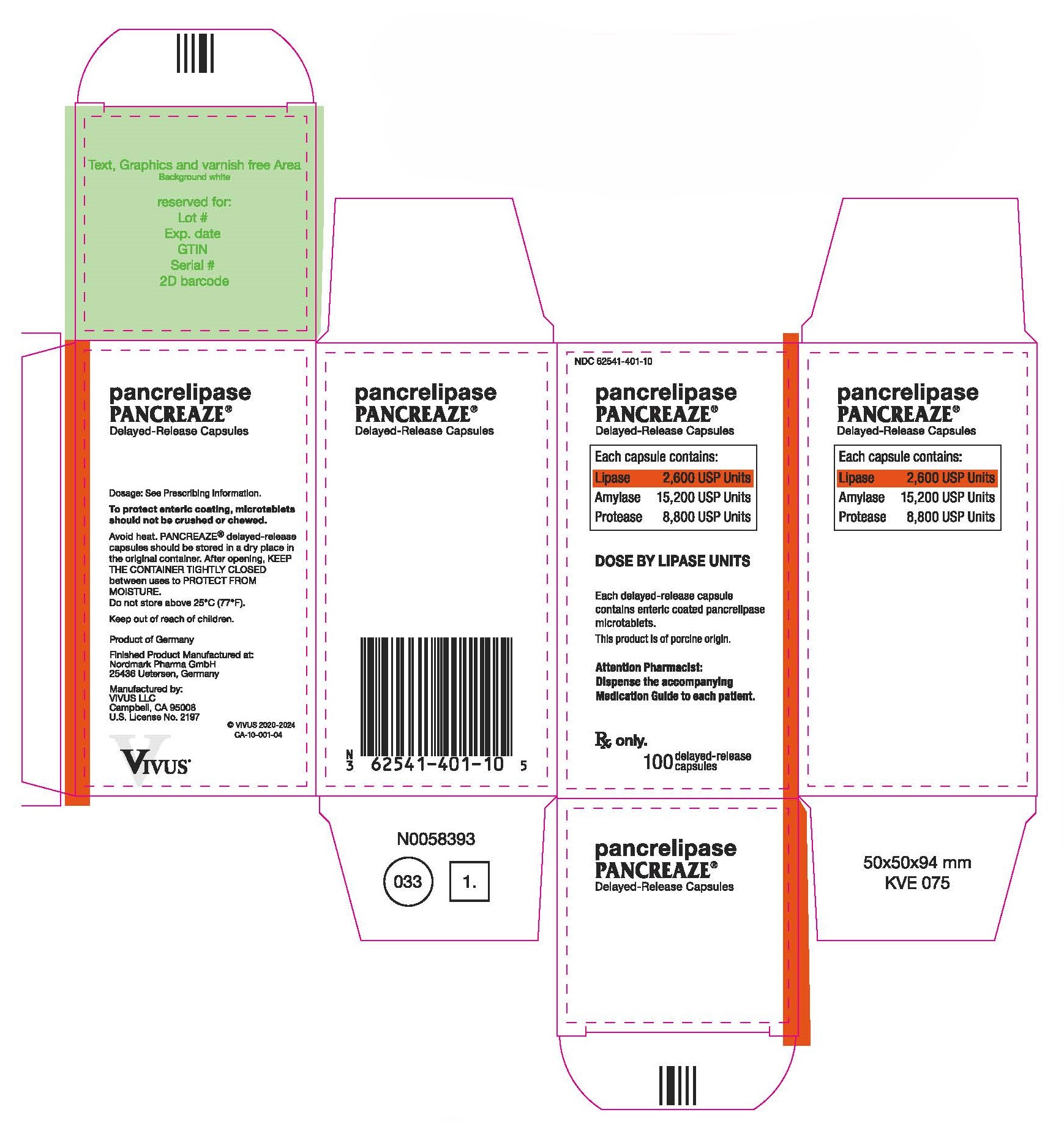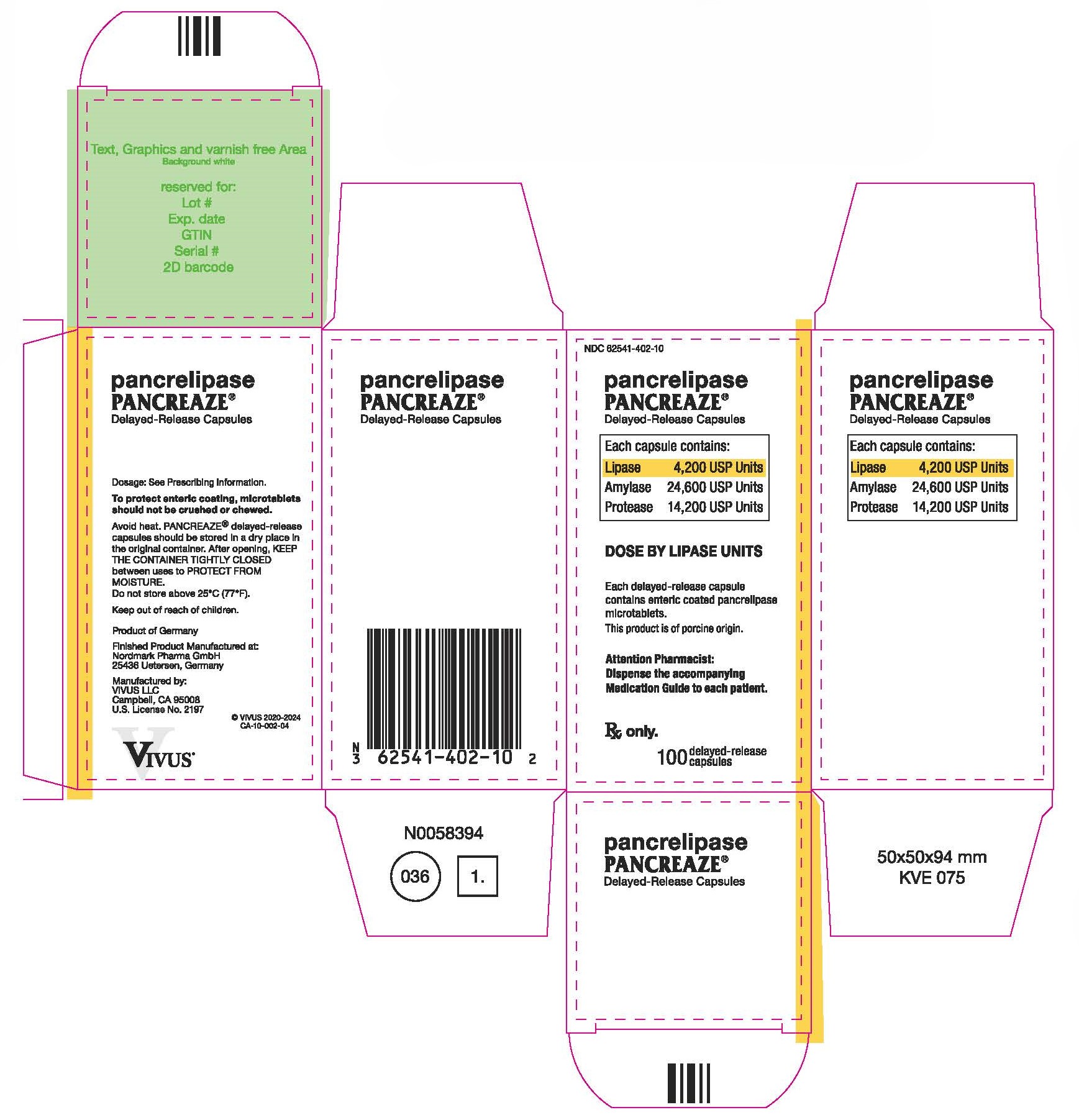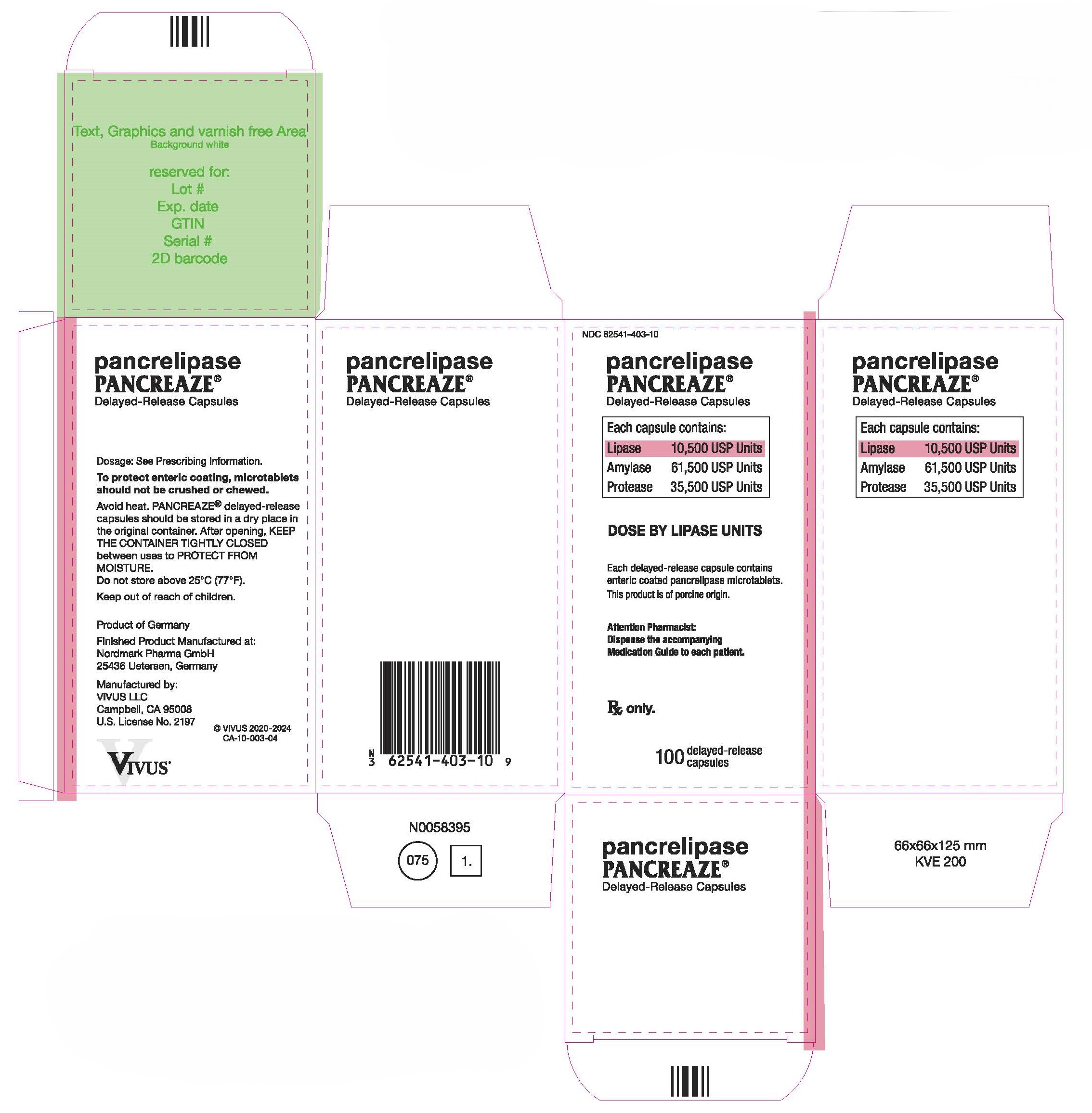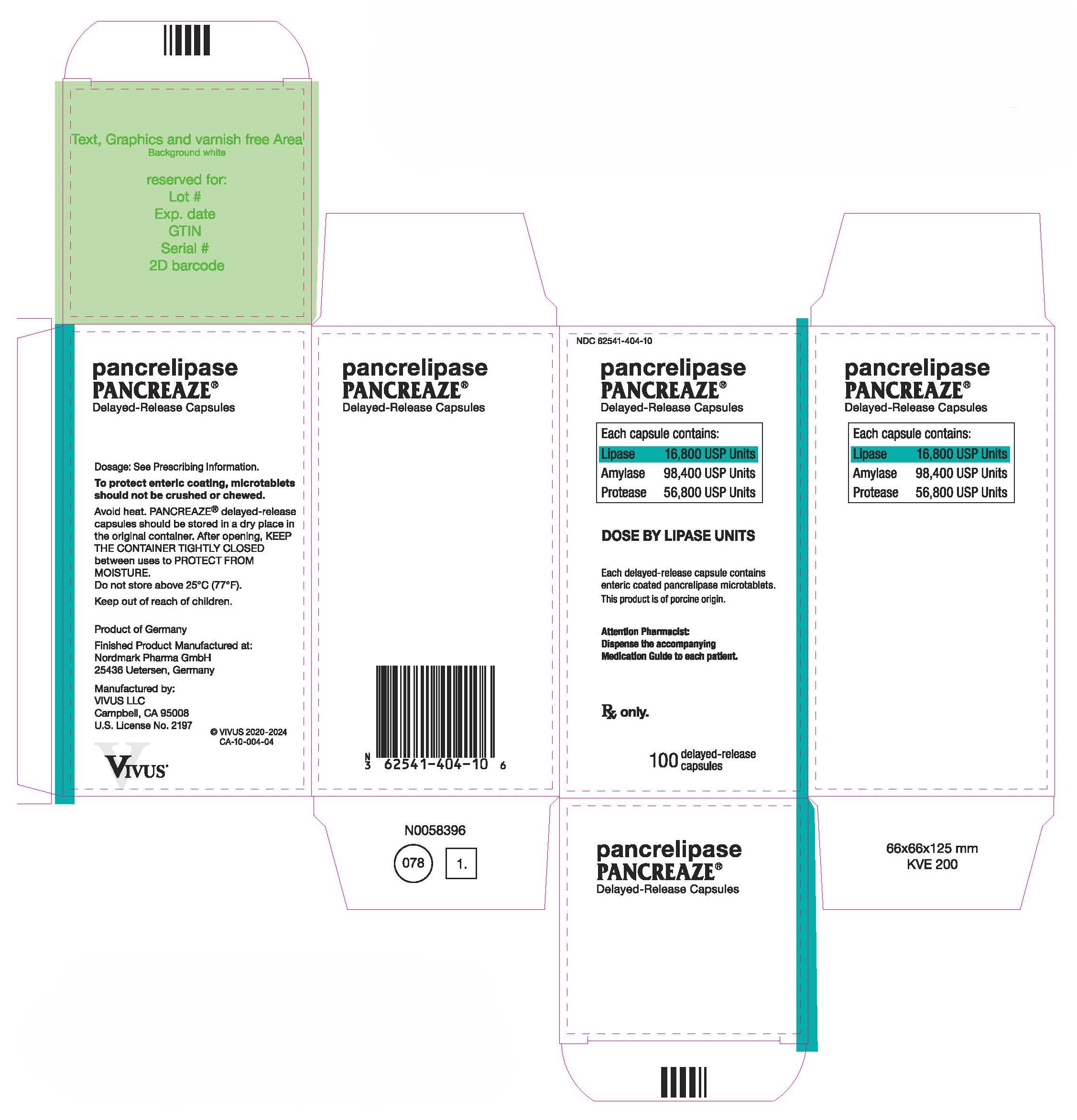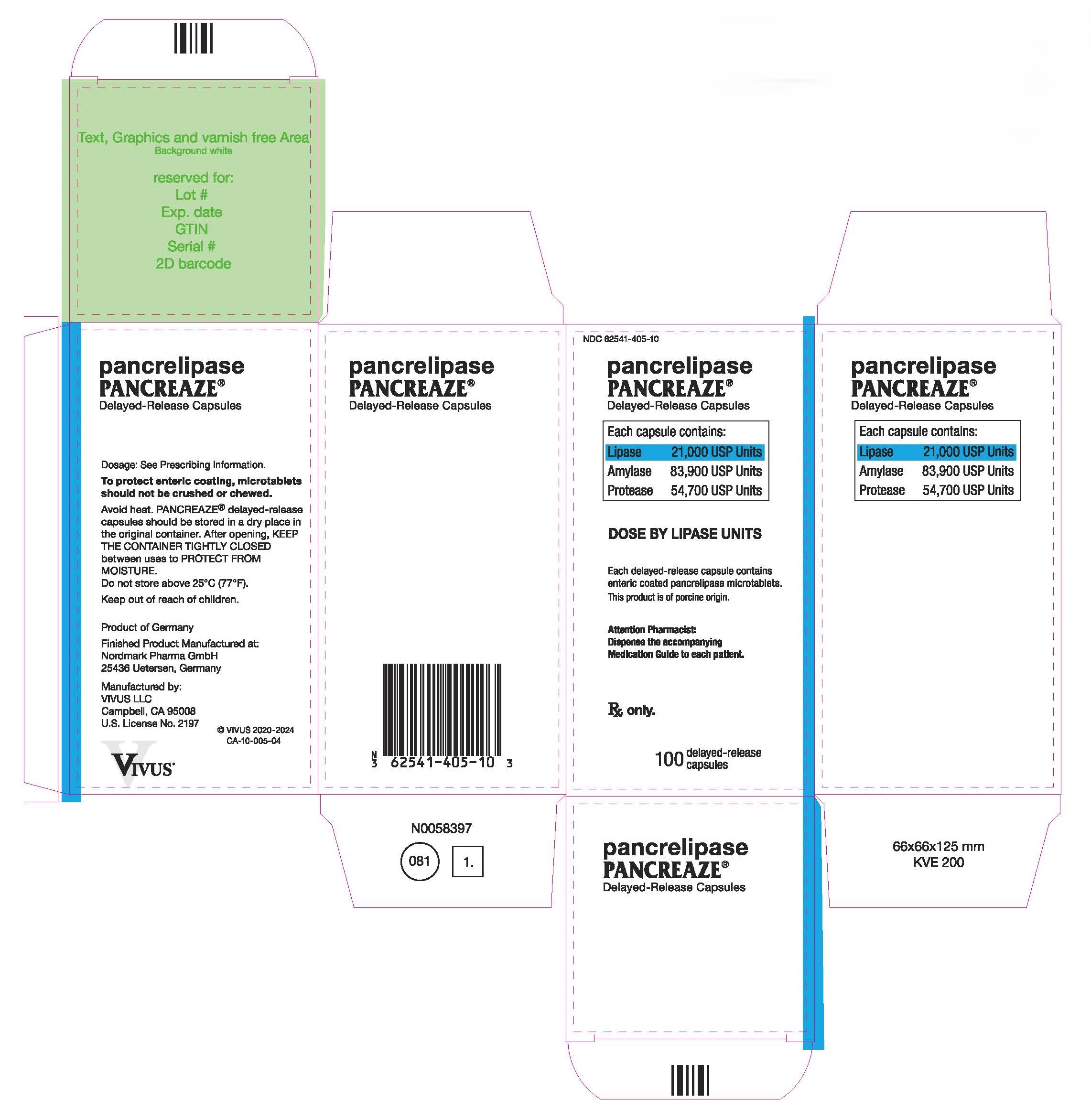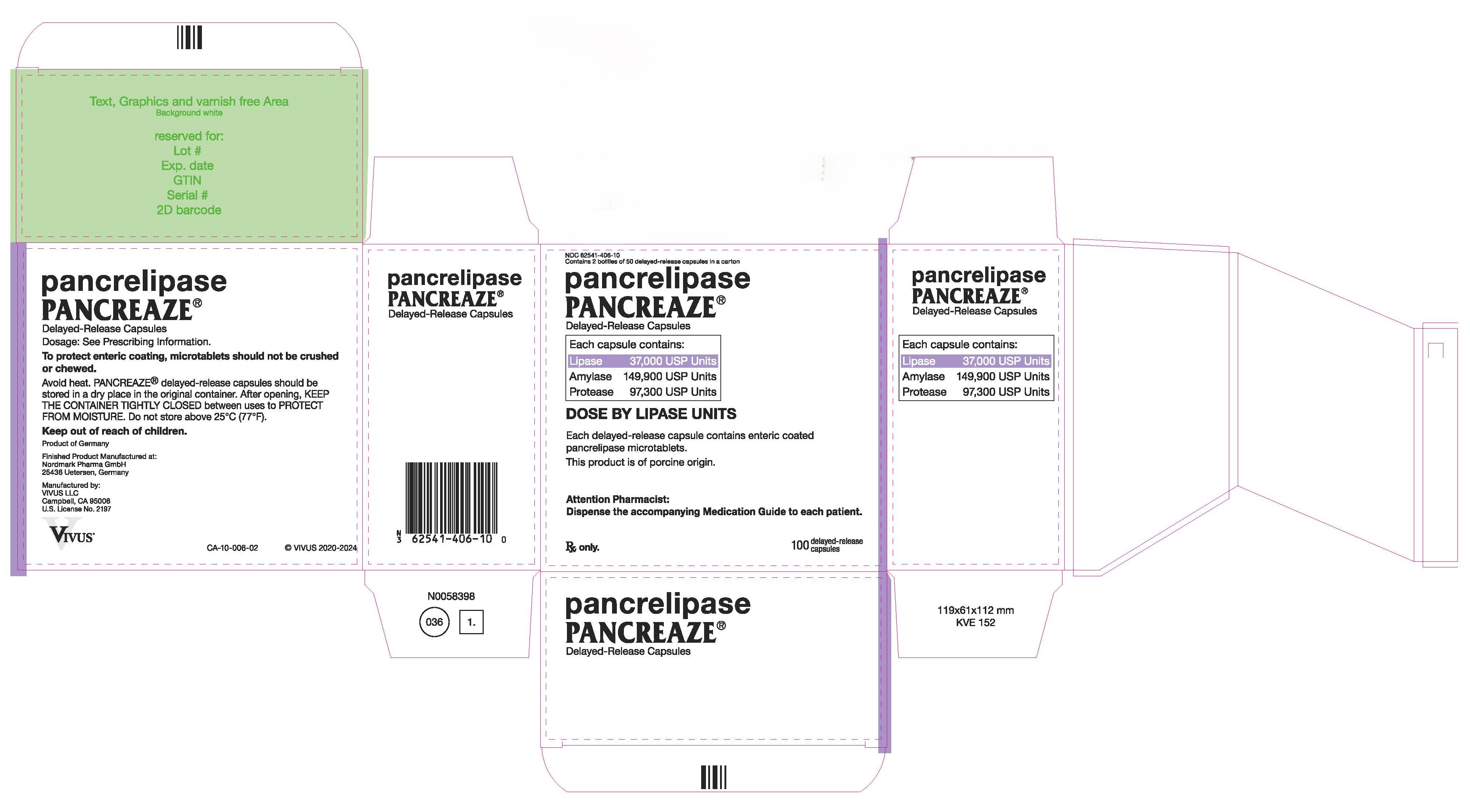 DRUG LABEL: PANCREAZE
NDC: 62541-402 | Form: CAPSULE, DELAYED RELEASE
Manufacturer: VIVUS LLC
Category: prescription | Type: HUMAN PRESCRIPTION DRUG LABEL
Date: 20250606

ACTIVE INGREDIENTS: PANCRELIPASE LIPASE 4200 [USP'U]/1 1; PANCRELIPASE AMYLASE 24600 [USP'U]/1 1; PANCRELIPASE PROTEASE 14200 [USP'U]/1 1
INACTIVE INGREDIENTS: CROSPOVIDONE (120 .MU.M); SILICON DIOXIDE; MAGNESIUM STEARATE; METHACRYLIC ACID AND ETHYL ACRYLATE COPOLYMER; TRIETHYL CITRATE; TALC; DIMETHICONE; HYPROMELLOSE, UNSPECIFIED; TITANIUM DIOXIDE; SODIUM LAURYL SULFATE; SORBITAN MONOLAURATE; MICROCRYSTALLINE CELLULOSE; FERRIC OXIDE YELLOW; SHELLAC; AMMONIA; PROPYLENE GLYCOL; FERROSOFERRIC OXIDE

HIGHLIGHTS OF PRESCRIBING INFORMATION

These highlights do not include all the information needed to use PANCREAZE® safely and effectively. See full prescribing information for PANCREAZE®.
PANCREAZE® (pancrelipase) delayed-release capsules
Initial U.S. Approval: 2010

1 INDICATIONS AND USAGE

PANCREAZE® is indicated for the treatment of exocrine pancreatic insufficiency in adult and pediatric patients. (1)

2 DOSAGE AND ADMINISTRATION

Important Dosing Information (2.1)

- PANCREAZE is a mixture of enzymes including lipases, proteases, and amylases and dosing is based on lipase units. Dosing scheme based on actual body weight or fat ingestion.
- Individualize the dosage based on clinical symptoms, the degree of steatorrhea present, and the fat content of the diet.
- Do not exceed 2,500 lipase units/kg/meal, 10,000 lipase units/kg/day, or 4,000 lipase units/g fat ingested/day in adult and pediatric patients greater than 12 months of age without further investigation. (5.1)
- The total daily dosage in adult and pediatric patients greater than 12 months of age should reflect approximately three meals plus two or three snacks per day. With each snack, administer approximately half the prescribed dose for a meal.
- Do not substitute other pancreatic enzyme products for PANCREAZE. When switching from another pancreatic enzyme product to PANCREAZE, monitor patients for clinical symptoms of exocrine pancreatic insufficiency and titrate the dosage as needed.

Recommended Dosage (2.2):

Adult and Pediatric Patients Greater than 12 Months: The recommended initial starting dosage is:

- 500 lipase units/kg/meal for adult and pediatric patients 4 years and older.
- 1,000 lipase units/kg/meal for pediatric patients greater than 12 months to less than 4 years.
- Titrate the dosage to either 2,500 lipase units/kg/meal, 10,000 lipase units/kg/day, or less than 4,000 lipase units/g fat ingested/day. Higher dosages may be administered if documented effective by fecal fat measures or improvement in malabsorption.

Pediatric Patients Birth to 12 Months: The recommended dosage is 2,600 lipase units (one capsule) per 120 mL of formula or per breastfeeding.

Preparation and Administration Instructions (2.3)

- Swallow capsules whole. For patients unable to swallow intact capsule(s), the capsule contents may be sprinkled on soft acidic food (e.g., applesauce).
- Do not crush or chew PANCREAZE capsules or capsule contents.
- Consume sufficient liquids to ensure complete swallowing of PANCREAZE. (5.2)
- See the full prescribing information for additional information on administering to pediatric patients birth to 12 months.

3 DOSAGE FORMS AND STRENGTHS

Delayed-release capsules (3):

- 2,600 USP units of lipase; 8,800 USP units of protease; and 15,200 USP units of amylase.
- 4,200 USP units of lipase; 14,200 USP units of protease; and 24,600 USP units of amylase
- 10,500 USP units of lipase; 35,500 USP units of protease; and 61,500 USP units of amylase
- 16,800 USP units of lipase; 56,800 USP units of protease; and 98,400 USP units of amylase
- 21,000 USP units of lipase; 54,700 USP units of protease; and 83,900 USP units of amylase
- 37,000 USP units of lipase; 97,300 USP units of protease; and 149,900 USP units of amylase

4 CONTRAINDICATIONS

None.

5 WARNINGS AND PRECAUTIONS

- Fibrosing Colonopathy: Associated with high doses, usually over prolonged use and in pediatric patients with cystic fibrosis. Colonic stricture reported in pediatric patients less than 12 years of age with dosages exceeding 6,000 lipase units/kg/meal. Monitor during treatment for progression of preexisting disease. Do not exceed the recommended dosage, unless clinically indicated. (2.1, 5.1)
- Irritation of the Oral Mucosa: May occur due to loss of protective enteric coating on the capsule contents. (2.3, 5.3)
- Hyperuricemia: Reported with high dosages; consider monitoring blood uric acid levels in patients with gout, renal impairment, or hyperuricemia. (5.3)
- Risk of Viral Transmission: The presence of porcine viruses that might infect humans cannot be definitely excluded. (5.4)
- Hypersensitivity Reactions: Monitor patients with known reactions to proteins of porcine origin. If symptoms occur, initiate appropriate medical management; consider the risks and benefits of continued treatment. (5.5)

6 ADVERSE REACTIONS

Most common adverse reactions are gastrointestinal, including nausea and vomiting. (6)

To report SUSPECTED ADVERSE REACTIONS, contact VIVUS LLC at 1-888-998-4887 or FDA at 1-800-FDA-1088 or www.fda.gov/medwatch

FULL PRESCRIBING INFORMATION

1 INDICATIONS AND USAGE

PANCREAZE is indicated for the treatment of exocrine pancreatic insufficiency in adult and pediatric patients.

2 DOSAGE AND ADMINISTRATION

2.1 Important Dosing Information

PANCREAZE is a mixture of enzymes including lipases, proteases, and amylases. PANCREAZE dosing is based on lipase units.

- Use either an actual body weight or fat ingestion-based dosing scheme.
- Start at the lowest recommended dosage and individualize the dosage based on clinical symptoms, the degree of steatorrhea present, and the fat content of the diet. Changes in dosage may require an adjustment period of several days.
- Do not exceed 2,500 lipase units/kg/meal, 10,000 lipase units/kg/day, or 4,000 lipase units/g fat ingested/day in adult and pediatric patients greater than 12 months of age without further investigation [see Warnings and Precautions (5.1)] .
- The total daily dosage in adult and pediatric patients greater than 12 months of age should reflect approximately three meals plus two or three snacks per day. With each snack, administer approximately half the prescribed PANCREAZE dose for a meal.
- Do not substitute other pancreatic enzyme products for PANCREAZE. When switching from another pancreatic enzyme product to PANCREAZE, monitor patients for clinical symptoms of exocrine pancreatic insufficiency and titrate the dosage as needed.

2.2 Recommended Dosage

Adult and Pediatric Patients Greater than 12 Months of Age

The recommended oral initial starting dosage is:

- 500 lipase units/kg/meal for adult and pediatric patients 4 years of age and older.
- 1,000 lipase units/kg/meal for pediatric patients greater than 12 months to less than 4 years of age.
- If signs and symptoms of malabsorption persist, increase the dosage. Titrate to either 2,500 lipase units/kg/meal, 10,000 lipase units/kg/day, or less than 4,000 lipase units/grams of fat ingested/day.
- Higher dosages may be administered if they are documented to be effective by fecal fat measures or an improvement in signs and symptoms of malabsorption including measures of nutritional status.

Pediatric Patients Birth to 12 Months of Age

The recommended oral dosage is 2,600 lipase units per 120 mL of formula or per breast-feeding.

2.3 Preparation and Administration Instructions

Instruct adult and pediatric patients greater than 12 months of age, or their caregivers, of the following:

- Take PANCREAZE with meals or snacks. If a dose is missed, take the next dose with the next meal or snack.
- Swallow capsules whole.
- For patients who are unable to swallow intact capsules, carefully open the capsules and sprinkle the entire contents on a small amount of acidic soft food with a pH of 4.5 or less (e.g., applesauce). Consume the entire mixture immediately.
- Do not crush or chew PANCREAZE capsules or capsule contents.
- Consume sufficient liquids (water or juice) to ensure complete swallowing of PANCREAZE capsules [see Warnings and Precautions (5.2)] .

Instruct caregivers of pediatric patients birth to 12 months of age of the following:

- Immediately prior to each breast-feeding session or each administration of 120 mL of formula, carefully open one PANCREAZE capsule (containing 2,600 USP units of lipase) and administer the entire contents using one of the following two methods:
  - Sprinkle on a small amount of acidic soft food with a pH of 4.5 or less (e.g., applesauce) being careful not to crush the capsule contents. The entire mixture should be given to the infant immediately.
  - Sprinkle the capsule contents directly into the infant's mouth.
- Immediately administer additional breast milk or formula after PANCREAZE to ensure complete swallowing of the capsule contents.
- Do not mix PANCREAZE capsule contents directly into a bottle of breast milk or formula.
- Do not crush PANCREAZE capsule contents, and visually inspect the infant's mouth to ensure that no drug is retained in the mouth [see Warnings and Precautions (5.2)] .
- If a dose is missed, administer the next dose with the next feeding.

3 DOSAGE FORMS AND STRENGTHS

Delayed-release capsules are available in the following strengths:

- 2,600 USP units of lipase; 8,800 USP units of protease; and 15,200 USP units of amylase in a two-piece hypromellose capsule with a light orange opaque body and clear cap, printed with "VIVUS" and "MT 2"
- 4,200 USP units of lipase; 14,200 USP units of protease; and 24,600 USP units of amylase in a two-piece hypromellose capsule with a yellow opaque body and clear cap, printed with "VIVUS" and "MT 4"
- 10,500 USP units of lipase; 35,500 USP units of protease; and 61,500 USP units of amylase in a two-piece hypromellose capsule with a flesh opaque body and clear cap, printed with "VIVUS" and "MT 10"
- 16,800 USP units of lipase; 56,800 USP units of protease; and 98,400 USP units of amylase in a two-piece hypromellose capsule with a flesh opaque body and clear cap, printed with "VIVUS" and "MT 16"
- 21,000 USP units of lipase; 54,700 USP units of protease; and 83,900 USP units of amylase in a two-piece hypromellose capsule with a white opaque body and cap, printed with "VIVUS" and "MT 20"
- 37,000 USP units of lipase; 97,300 USP units of protease; and 149,900 USP units of amylase in a two-piece hypromellose capsule with an iron grey opaque body and white opaque cap, printed with "VIVUS" and "MT 37"

4 CONTRAINDICATIONS

None.

5 WARNINGS AND PRECAUTIONS

5.1 Fibrosing Colonopathy

Fibrosing colonopathy has been reported following treatment with pancreatic enzyme products. Fibrosing colonopathy is a rare, serious adverse reaction initially described in association with use of high-dose pancreatic enzyme products, usually over a prolonged period of time and most commonly reported in pediatric patients with cystic fibrosis. Pancreatic enzyme products exceeding 6,000 lipase units/kg/meal have been associated with colonic strictures, a complication of fibrosing colonopathy, in pediatric patients less than 12 years of age. The underlying mechanism of fibrosing colonopathy remains unknown.

If there is a history of fibrosing colonopathy, monitor patients during treatment with PANCREAZE because some patients may be at risk of progressing to colonic stricture formation. It is uncertain whether regression of fibrosing colonopathy occurs. Do not exceed the recommended dosage of either 2,500 lipase units/kg/meal, 10,000 lipase units/kg/day, or 4,000 lipase units/g fat ingested/day in adult and pediatric patients greater than 12 months of age without further investigation . Higher dosages may be administered if they are documented to be effective by fecal fat measures or an improvement in signs and symptoms of malabsorption including measures of nutritional status . Patients receiving dosages higher than 6,000 lipase units/kg/meal should be frequently monitored for symptoms of fibrosing colonopathy and the dosage decreased or titrated downward to a lower range if clinically appropriate [see Dosage and Administration (2.1)] .

5.2 Irritation of the Oral Mucosa

Crushing or chewing PANCREAZE capsules or mixing the capsule contents in foods having a pH greater than 4.5 can disrupt the protective enteric coating on the capsule contents and result in early release of enzymes, irritation of the oral mucosa, and/or loss of enzyme activity.

Instruct the patient or caregiver of the following:

- Swallow capsules whole. For patients who cannot swallow the capsules whole, the capsules can be opened, and the contents sprinkled on a small amount of acidic soft food with a pH of 4.5 or less (e.g., applesauce).
- Do not crush or chew PANCREAZE capsules or capsule contents.
- Consume sufficient liquids (juice, water, breast milk, or formula) immediately following administration of PANCREAZE to ensure complete swallowing.
- Visually inspect the mouth of pediatric patients less than 12 months of age and of patients who are unable to swallow intact capsules to ensure that no drug is retained in the mouth and irritation of the oral mucosa has not occurred [see Dosage and Administration (2.3)] .

5.3 Hyperuricemia

Pancreatic enzyme products contain purines that may increase blood uric acid levels. High dosages have been associated with hyperuricosuria and hyperuricemia [see Overdosage (10)]. Consider monitoring blood uric acid levels in patients with gout, renal impairment, or hyperuricemia during treatment with PANCREAZE.

5.4 Risk of Viral Transmission

PANCREAZE is sourced from pancreatic tissue from swine used for food consumption. Although the risk that PANCREAZE will transmit an infectious agent to humans has been reduced by testing for certain viruses during manufacturing and by inactivating certain viruses during manufacturing, there is a theoretical risk for transmission of viral disease, including diseases caused by novel or unidentified viruses. Thus, the presence of porcine viruses that might infect humans cannot be definitely excluded. However, no cases of transmission of an infectious illness associated with the use of porcine pancreatic extracts have been reported.

5.5 Hypersensitivity Reactions

Serious hypersensitivity reactions including anaphylaxis, asthma, hives, and pruritus have been reported with pancreatic enzyme products [see Adverse Reactions (6)] . If symptoms occur, initiate appropriate medical management.

Monitor patients with a known hypersensitivity reaction to proteins of porcine origin for hypersensitivity reactions during treatment with PANCREAZE. The risks and benefits of continued PANCREAZE treatment in patients with serious hypersensitivity reactions should be taken into consideration with the overall clinical needs of the patient.

6 ADVERSE REACTIONS

The following serious or otherwise important adverse reactions are described elsewhere in the labeling:

- Fibrosing Colonopathy [see Warnings and Precautions (5.1)]
- Irritation of the Oral Mucosa [see Warnings and Precautions (5.2)]
- Hyperuricemia [see Warnings and Precautions (5.3)]
- Risk of Viral Transmission [see Warnings and Precautions (5.4)]
- Hypersensitivity Reactions [see Warnings and Precautions (5.5)]

The data described below reflect exposure to PANCREAZE in 57 adult and pediatric patients with exocrine pancreatic insufficiency due to cystic fibrosis in two clinical trials. Study 1 was conducted in 40 patients, aged 8 years to 57 years; Study 2 was conducted in 17 pediatric patients, aged 6 months to 30 months [see Clinical Studies (14)] . The most common adverse reactions were gastrointestinal, including diarrhea and vomiting.

The following adverse reactions have been identified during post-approval use of PANCREAZE or other pancreatic enzyme products. Because these reactions are reported voluntarily from a population of uncertain size, it is not always possible to reliably estimate their frequency or establish a causal relationship to drug exposure.

Eye Disorders

- blurred vision

Gastrointestinal Disorders

- fibrosing colonopathy, distal intestinal obstruction syndrome
- abdominal pain, flatulence, constipation, and nausea

Immune System Disorders

- anaphylaxis, asthma, hives, and pruritus

Investigations

- asymptomatic elevations of liver enzymes

Musculoskeletal System

- myalgia, muscle spasm

Skin and Subcutaneous Tissue Disorders

- urticaria and rash

8 USE IN SPECIFIC POPULATIONS

8.1 Pregnancy

Risk Summary

Published data from case reports with pancrelipase use in pregnant women have not identified a drug-associated risk of major birth defects, miscarriage or other adverse maternal or fetal outcomes. Pancrelipase is minimally absorbed systematically; therefore, maternal use is not expected to result in fetal exposure to the drug. Animal reproduction studies have not been conducted with pancrelipase.

The background risk of major birth defects and miscarriage for the indicated population is unknown. All pregnancies have a background risk of birth defect, loss, or other adverse outcomes. In the U.S. general population, the estimated background risk of major birth defects and miscarriage in clinically recognized pregnancies is 2 to 4% and 15 to 20%, respectively.

8.2 Lactation

Risk Summary

There are no data on the presence of pancrelipase in either human or animal milk, the effects on the breastfed infant or the effects on milk production. Pancrelipase is minimally absorbed systemically following oral administration, therefore maternal use is not expected to result in clinically relevant exposure of breastfed infants to the drug. The developmental and health benefits of breastfeeding should be considered along with the mother's clinical need for PANCREAZE and any potential adverse effects on the breastfed infant from PANCREAZE or from the underlying maternal condition.

8.4 Pediatric Use

The safety and effectiveness of PANCREAZE for the treatment of exocrine pancreatic insufficiency have been established in pediatric patients.

Use of PANCREAZE for this indication is supported by an adequate and well-controlled trial in adult and pediatric patients 8 to 17 years of age (Study 1) along with supportive data from a randomized, investigator-blinded, dose-ranging study in 17 pediatric patients aged 6 to 30 months (Study 2). Both study populations consisted of patients with exocrine pancreatic insufficiency due to cystic fibrosis. The safety in pediatric patients in these studies was similar to that observed in adult patients [see Adverse Reactions (6) and Clinical Studies (14)] .

Dosages exceeding 6,000 lipase units/kg/meal have been reported postmarketing to be associated with fibrosing colonopathy and colonic strictures in pediatric patients less than 12 years of age. If there is a history of fibrosing colonopathy, monitor patients during treatment with PANCREAZE because some patients may be at risk of progressing to stricture formation. Do not exceed the recommended dosage of either 2,500 lipase units/kg/meal, 10,000 lipase units/kg/day, or 4,000 lipase units/g fat ingested/day in pediatric patients greater than 12 months of age without further investigation . [see Dosage and Administration (2.2) and Warnings and Precautions (5.1)] .

Crushing or chewing PANCREAZE capsules or mixing the capsule contents in foods having a pH greater than 4.5 can disrupt the protective enteric coating on the capsule contents and result in early release of enzymes, irritation of the oral mucosa, and/or loss of enzyme activity. Instruct the patient or caregiver of the following: consume sufficient liquids (juice, water, breast milk, or formula) to ensure complete swallowing, and visually inspect the mouth of pediatric patients less than 12 months of age to ensure no drug is retained in the mouth and irritation of the oral mucosa has not occurred [see Dosage and Administration (2.3) and Warnings and Precautions (5.2)].

8.5 Geriatric Use

Clinical studies of PANCREAZE did not include sufficient numbers of patients aged 65 years and over to determine whether they respond differently from younger patients. Other reported clinical experience has not identified differences in responses between patients aged 65 years and over and younger adult patients.

10 OVERDOSAGE

In Study 1, a 10 year-old patient was administered a PANCREAZE dose of 12,399 lipase units/kg/day for the duration of the open-label and randomized withdrawal periods (21 days). The patient experienced mild abdominal pain throughout both study periods. Abnormal chemistry data at the end of the study included mild elevations of aspartate aminotransferase (AST), alanine aminotransferase (ALT), and serum phosphate. Abnormal hematology data at the end of the study included mild elevations of hematocrit. No abnormalities from analyses of urinalysis or uric acid were noted.

Chronic high dosages of pancreatic enzyme products have been associated with fibrosing colonopathy and colonic strictures [see Warnings and Precautions (5.1)] . High dosages of pancreatic enzyme products have been associated with hyperuricosuria and hyperuricemia [see Warnings and Precautions (5.3)] .

11 DESCRIPTION

Pancrelipase is a pancreatic enzyme product consisting of a mixture of enzymes including lipases, proteases, and amylases and is an extract derived from porcine pancreatic glands. The enteric-coated microtablets in PANCREAZE are formulated to release pancreatic enzymes at an approximate pH of 5.5 or greater.

PANCREAZE (pancrelipase) delayed-release capsules are for oral administration and include a two-piece shell containing enteric-coated microtablets that are each approximately 2 mm in diameter and are available as follows:

2,600 USP units of lipase; 8,800 USP units of protease; and 15,200 USP units of amylase; delayed-release capsules have a light orange opaque body and clear cap imprinted with "VIVUS" and "MT 2". The shells contain hypromellose, titanium dioxide, yellow iron oxide, red iron oxide and imprint ink contains black iron oxide, shellac, propylene glycol, strong ammonia solution, potassium hydroxide.

4,200 USP units of lipase; 14,200 USP units of protease; and 24,600 USP units of amylase; delayed-release capsules have a yellow opaque body and clear cap imprinted with "VIVUS" and "MT 4". The shells contain hypromellose, titanium dioxide, yellow iron oxide, and imprint ink contains black iron oxide, shellac-glaze-45%, ammonium hydroxide, propylene glycol.

10,500 USP units of lipase; 35,500 USP units of protease; and 61,500 USP units of amylase; delayed-release capsules have a flesh opaque body and clear cap imprinted with "VIVUS" and "MT 10". The shells contain hypromellose, titanium dioxide, red iron oxide, and imprint ink contains black iron oxide, shellac-glaze-45%, ammonium hydroxide, propylene glycol.

16,800 USP units of lipase; 56,800 USP units of protease; 98,400 USP units of amylase; delayed-release capsules have a flesh opaque body and clear cap imprinted with "VIVUS" and "MT 16". The shells contain hypromellose, titanium dioxide, red iron oxide, yellow iron oxide, and imprint ink contains black iron oxide, shellac-glaze-45%, ammonium hydroxide, propylene glycol.

21,000 USP units of lipase; 54,700 USP units of protease; and 83,900 USP units of amylase; delayed-release capsules have a white opaque body and cap imprinted with "VIVUS" and "MT 20". The shells contain hypromellose, titanium dioxide, and imprint ink contains yellow iron oxide, shellac, strong ammonia solution, propylene glycol.

37,000 USP units of lipase; 97,300 USP units of protease; and 149,900 USP units of amylase; delayed-release capsules have an iron grey opaque body and white opaque cap imprinted with "VIVUS" and "MT 37". The shells contain hypromellose, titanium dioxide, black iron oxide and imprint ink contains black iron oxide, shellac-glaze-45%, ammonium hydroxide, propylene glycol.

PANCREAZE (pancrelipase) delayed-release capsules include the following inactive ingredients: colloidal silicon dioxide, crospovidone, magnesium stearate, methacrylic acid ethyl acrylate copolymer, microcrystalline cellulose, montan glycol wax, simethicone emulsion, talc and triethyl citrate.

12 CLINICAL PHARMACOLOGY

12.1 Mechanism of Action

Pancreatic enzyme products contain a mixture of lipases, proteases, and amylases that catalyze the hydrolysis of fats to monoglyceride, glycerol and free fatty acids, proteins into peptides and amino acids, and starches into dextrins and short chain sugars such as maltose and maltriose in the duodenum and proximal small intestine, thereby acting like digestive enzymes physiologically secreted by the pancreas.

12.2 Pharmacodynamics

For patients consuming a high fat diet in the clinical trials, the coefficient of fat absorption (CFA) was higher in patients who received PANCREAZE compared to the placebo treatment group, indicating improved fat absorption [see Clinical Studies (14)] .

12.3 Pharmacokinetics

Following oral administration, the lipases, proteases, and amylases released from PANCREAZE are not absorbed from the gastrointestinal tract in appreciable amounts.

Drug Interactions

The lipases, proteases, and amylases of PANCREAZE are not substrates of CYP enzymes or transporters. CYP enzymes or transporters mediated drug interactions are not expected.

14 CLINICAL STUDIES

Studies 1 and 2 were conducted in 57 adult and pediatric patients, aged 6 months to 17 years, with exocrine pancreatic insufficiency due to cystic fibrosis.

Study 1

Study 1 was a randomized, double-blind, placebo-controlled study of 40 patients, ages 8 to 57 years. In this study, patients received PANCREAZE at individually titrated doses (not to exceed 2,500 lipase units/kg/meal) for 14 days (open-label period) followed by randomization to PANCREAZE or matching placebo for 7 days of treatment (double-blind withdrawal period). Only patients with coefficient of fat absorption (CFA) ≥80% in the open-label period were randomized to the double-blind withdrawal period. The mean dosage during the 70day placebo-controlled treatment period was 6,400 lipase units/kg/day. All patients consumed a high-fat diet (greater than or equal to 100 grams of fat per day) during the treatment period. The population was nearly evenly distributed in biological sex and approximately 96% of patients were White.

Coefficient of Fat Absorption Endpoint and Results

The primary efficacy endpoint was the change in CFA from the open label period to the end of the double-blind withdrawal period. The CFA was determined by a 72-hour stool collection period during both treatment periods, when both fat excretion and fat ingestion were measured (Table 1).

Table 1. Change in CFA in Study 1 (Open-Label Period to End of Double-Blind Withdrawal Period)
 | PANCREAZE N=20 | Placebo N=20
CFA [%]
Open-Label Period [Minimum of 72 hours from start of open label period.] (Mean, SD) | 88 (5) | 91 (5)
End of Double-Blind Withdrawal Period [Double-blind withdrawal period ranged from 4 to 7 days.] (Mean, SD) | 87 (8) | 56 (25)
Change in CFA [p<0.001] [%]
Open-Label Period to End of Double-Blind Withdrawal Period (Mean, SD) | -2 (6) | -34 (23)
Treatment Difference Point Estimate (95% CI) | 33 (25, 40)

At the end of the double-blind withdrawal period, the mean change in CFA from the open-label period to the end of the double-blind withdrawal period was -2% with PANCREAZE treatment compared to -34% with placebo treatment. There were similar responses to PANCREAZE by age and biological sex.

Study 2

Study 2 was a randomized, investigator-blinded, dose-ranging study of 17 pediatric patients, ages 6 months to 30 months (mean 18 months). The final analysis population was limited to 16 patients; 1 patient was excluded due to withdrawal of consent. All patients were transitioned from their usual pancreatic enzyme treatment to PANCREAZE at 375 lipase units/kg/meal for a 6-day run-in period. Patients were then randomized to receive PANCREAZE at one of four dosages (375, 750, 1,125, and 1,500 lipase units/kg/meal) for 5 days.

Coefficient of Fat Absorption Endpoint and Results

The CFA was measured at the end of the run-in period and at the end of the randomized period (Table 2).

Table 2. Change in CFA in Study 2 (End of Run-in Period to End of Study)
 | 375 lipase units/kg/meal N=4 | 750 lipase units/kg/meal N=4 | 1,125 lipase units/kg/meal N=4 | 1,500 lipase units/kg/meal N=4
CFA (%)
Day 6 [End of Run-in Period;] (Mean, SD) | 93 (2) | 90 (5) | 81 (11) | 93 (3)
Day 11 [End of Study] (Mean, SD) | 92 (3) | 91 (4) | 80 (13) | 91 (2)
Change in CFA (%)
Day 6 to Day 11 (Mean, SD) | -2 (3) | 1 (3) | -1 (3) | -2 (3)

Overall, patients showed similar CFA at the end of the run-in period (mean PANCREAZE dosage of 1,600 lipase units/kg/day) and at the end of the study across the four treatment arms.

16 HOW SUPPLIED/STORAGE AND HANDLING

PANCREAZE (pancrelipase) delayed-release capsules are supplied as follows:

Strength | Description | Supplied As NDC Number
2,600 USP units of lipase; 8,800 USP units of protease; 15,200 USP units of amylase | two-piece hypromellose capsule with a light orange opaque body and clear cap imprinted with "VIVUS" and "MT 2" | Bottles of 100 NDC 62541-401-10
4,200 USP units of lipase; 14,200 USP units of protease; 24,600 USP units of amylase | two-piece hypromellose capsule with a yellow opaque body and clear cap imprinted with "VIVUS" and "MT 4" | Bottles of 100 NDC 62541-402-10
10,500 USP units of lipase; 35,500 USP units of protease; 61,500 USP units of amylase | two-piece hypromellose capsule with a pink opaque body and clear cap imprinted with "VIVUS" and "MT 10" | Bottles of 100 NDC 62541-403-10
16,800 USP units of lipase; 56,800 USP units of protease; 98,400 USP units of amylase | two-piece hypromellose capsule with a flesh opaque body and clear cap imprinted with "VIVUS" and "MT 16" | Bottles of 100 NDC 62541-404-10
21,000 USP units of lipase; 54,700 USP units of protease; 83,900 USP units of amylase | two-piece hypromellose capsule with a white opaque body and cap imprinted with "VIVUS" and "MT 20" | Bottles of 100 NDC 62541-405-10
37,000 USP units of lipase; 97,300 USP units of protease; 149,900 USP units of amylase | Two-piece hypromellose capsule with an iron grey opaque body and white opaque cap imprinted with "VIVUS" and "MT 37" amylase | 2 bottles of 50-(NDC 62541-406-50) inside a carton (NDC 62541-406-10)

Storage and Handling

Store PANCREAZE at room temperature between 15ºC and 25ºC (59°F to 77°F), excursion permitted up to 40ºC (104°F) for 24 hours.

After opening, keep bottle tightly closed between uses to protect from moisture.

All PANCREAZE bottles contain a desiccant canister.

Store and dispense PANCREAZE in the original container.

17 PATIENT COUNSELING INFORMATION

Advise the patient or caregiver to read the FDA-approved patient labeling (Medication Guide).

Fibrosing Colonopathy

Advise the patient or caregiver that fibrosing colonopathy has been reported with high dosages of pancreatic enzyme products, usually with use over a prolonged period of time and in pediatric patients with cystic fibrosis. Colonic stricture has been reported in pediatric patients less than 12 years of age. Advise patients and caregivers that if signs and symptoms of colon stricture formation occur (e.g., stomach area (abdominal) pain, bloating, trouble passing stool (constipation), nausea, vomiting, diarrhea) to immediately contact their healthcare provider [see Warnings and Precautions (5.1)] .

Hyperuricemia

Advise the patient or caregiver that hyperuricemia may occur in patients with gout or renal impairment and to contact the healthcare provider if they experience pain, stiffness, redness or swelling of their joints [see Warnings and Precautions (5.3)] .

Hypersensitivity Reactions

Inform the patient or caregiver that severe hypersensitivity reactions, including anaphylaxis asthma, hives, and pruritus, have been reported with use of pancreatic enzyme products. Seek medical attention if signs or symptoms of a hypersensitivity reaction develop [see Warnings and Precautions (5.5)] .

Dosage

Advise the patient or caregiver to take or administer PANCREAZE as prescribed, and to contact the healthcare provider if signs and symptoms of malabsorption persist [see Dosage and Administration (2.2)] .

Administration

Instruct the patient or caregiver to:

- Take PANCREAZE with meals or snacks.
- Swallow capsules whole.
- For adult and pediatric patients unable to swallow intact capsules, the capsule contents may be sprinkled on a small amount soft acidic food with a pH of 4.5 or less (e.g., applesauce). For pediatric patients birth to 12 months of age, PANCREAZE capsules can also be opened, and the capsule contents sprinkled directly into the infant's mouth.
- Consume sufficient liquids (juice, water, breast milk, or formula) and visually inspect an infant's mouth to ensure complete swallowing of PANCREAZE capsules or capsule contents [see Warnings and Precautions (5.2)].
- Do not crush or chew PANCREAZE capsules or capsule contents.
- Do not mix the PANCREAZE capsule contents directly into a bottle of breast milk or formula.

Storage

Instruct the patient or caregiver as follows:

- Keep PANCREAZE in a dry place and protect from moisture and heat.
- After opening, keep bottle tightly closed between uses to protect from moisture.
- Keep PANCREAZE in the original container.
- Do not eat or throw away the desiccant canister in the bottle.

Product of Germany

Finished Product Manufactured at:
Nordmark Pharma GmbH
25436 Uetersen, Germany.

Manufactured by:
VIVUS LLC
900 E. Hamilton Ave., Suite 550
Campbell, CA 95008 USA
© VIVUS LLC 2010-2024

MEDICATION GUIDE
PANCREAZE® (pan-kre-aze)
(pancrelipase)
delayed-release capsules

What is the most important information I should know about PANCREAZE?

PANCREAZE may increase your chance of having a rare bowel disorder called fibrosing colonopathy especially if taken at a high dose for a long time in children with cystic fibrosis. This condition is serious and may require surgery. The risk of having this condition may be reduced by following the dosing instructions that your doctor gave you. Call your doctor right away if you have any unusual or severe:

- stomach area (abdominal) pain
- bloating
- trouble passing stool (constipation)
- nausea, vomiting, or diarrhea

Take PANCREAZE exactly as prescribed by your doctor. Do not take more PANCREAZE than directed by your doctor.

What is PANCREAZE?
PANCREAZE is a prescription medicine used to treat people who cannot digest food normally because their pancreas does not make enough enzymes.
PANCREAZE contains a mixture of digestive enzymes including lipases, proteases, and amylases from pig pancreas.
PANCREAZE is safe and effective in adults and children.

Before taking PANCREAZE, tell your doctor about all your medical conditions, including if you:

- are allergic to pork (pig) products.
- have a history of blockage of your intestines, or scarring or thickening of your bowel wall (fibrosing colonopathy).
- have gout, kidney disease, or high blood uric acid (hyperuricemia).
- have trouble swallowing capsules.
- have any other medical condition.
- are pregnant or plan to become pregnant.
- are breastfeeding or plan to breastfeed. It is not known if PANCREAZE passes into your breast milk. Talk to your doctor about the best way to feed your baby if you take PANCREAZE.

Tell your doctor about all the medicines you take, including prescription and over-the-counter medicines, vitamins, or herbal supplements.
Know the medicines you take. Keep a list of them and show it to your doctor and pharmacist when you get a new medicine.

How should I take PANCREAZE?

- Take PANCREAZE exactly as your doctor tells you. Contact your doctor if you continue to have signs and symptoms of malabsorption (not absorbing nutrients from food) such as abdominal pain, bloating, fatty stools, or weight loss. Your dose may need to be changed.
- You should not switch PANCREAZE with any other pancreatic enzyme product without first talking to your doctor.
- Do not take more capsules in a day than the number your doctor tells you (total daily dose).
- Always take PANCREAZE with a meal or snack and enough liquid (water, juice breast milk, or formula) to swallow PANCREAZE completely. If you eat a lot of meals or snacks in a day, be careful not to go over your total daily dose.
- Your doctor may change your dose based on the amount of fatty foods you eat or based on your weight.
- PANCREAZE capsules should be swallowed whole. Do not crush or chew PANCREAZE capsules or its contents, and do not hold the capsule contents in your mouth. Crushing, chewing or holding the PANCREAZE capsules in your mouth may cause irritation in your mouth or change the way PANCREAZE works in your body.

Giving PANCREAZE to Infants (Children from Birth up to 12 Months of Age):
The two ways to give PANCREAZE to infants (children from birth to 12 months of age) are described below:

- Giving with Acidic Soft Food
  1. Before each breast-feeding session or each time you give 120 mL of formula, carefully open the capsule and sprinkle the entire contents of the capsule on a small amount of acidic food such as applesauce. These foods should be the kind found in baby food jars that you buy at the store, or other food recommended by your doctor.
  2. Mix the capsule contents evenly through the food. Be careful not to crush the PANCREAZE capsule contents while mixing.
  3. Give the PANCREAZE and food mixture to your infant right away. Do not store PANCREAZE that is mixed with food.
  4. Give your infant enough formula or breastfeed your infant right away to completely swallow the PANCREAZE food mixture.
  5. Look into your infant's mouth to make sure that all the medicine has been swallowed.
  6. Throw away the empty PANCREAZE capsule.
- Giving Directly Into Infant's Mouth Before Breast or Formula Feeding
  1. Before each breast-feeding session or each time you give 120 mL of formula, carefully open the PANCREAZE capsule and sprinkle the capsule contents directly into the infant's mouth.
  2. Do not mix the PANCREAZE capsule contents directly into a bottle of breast milk or formula.
  3. Give your infant additional breast milk or formula right after PANCREAZE to completely swallow the PANCREAZE capsule contents.
  4. Look into your infant's mouth to make sure that all the medicine has been swallowed.
  5. Throw away the empty PANCREAZE capsule.

- If a dose is missed, give the next dose with the next feeding.

Giving PANCREAZE to Adults and Children Older than 12 Months of Age:

- Swallow PANCREAZE capsules whole and take them with enough liquid (water or juice) to swallow them right away.
- If you have trouble swallowing capsules follow these instructions for taking PANCREAZE with food:
  - Carefully open the capsules and sprinkle the entire contents on a small amount of acidic food such as applesauce. Ask your doctor about other foods you can mix with PANCREAZE.
  - If you sprinkle PANCREAZE on food, swallow it right after you mix it and drink plenty of water or juice to make sure the medicine is swallowed completely. Do not store PANCREAZE that is mixed with food.
  - If you forget to take PANCREAZE, call your doctor or wait until your next meal and take your usual number of capsules. Take your next dose at your usual time. Do not make up for missed doses.

What are the possible side effects of PANCREAZE?
PANCREAZE may cause serious side effects, including:

- See "What is the most important information I should know about PANCREAZE?"
- Irritation of the inside of your mouth. This can happen if PANCREAZE is not swallowed completely.
- Increase in blood uric acid levels (hyperuricemia). This may happen in people with gout, kidney problems, or those who take high doses of pancrelipase, the active ingredient in PANCREAZE. Call your doctor if you have pain, stiffness, redness or swelling in your joints.
- Severe allergic reactions. Severe allergic reactions have happened in people taking pancreatic enzyme products like PANCREAZE. Stop taking PANCREAZE and get emergency treatment right away if you have any of these symptoms: trouble with breathing, skin rashes, swollen lips, or itching.

The most common side effects of PANCREAZE include:

- stomach (abdominal area) problems including nausea and vomiting.

Other possible side effects of PANCREAZE:
PANCREAZE and other pancreatic enzyme products are made from the pancreas of pigs, the same pigs people eat as pork. These pigs may carry viruses. Although it has never been reported, it may be possible for a person to get a viral infection from taking pancreatic enzyme products that come from pigs.
Tell your doctor if you have any side effect that bothers you or does not go away.
These are not all the possible side effects of PANCREAZE. For more information, ask your doctor or pharmacist.
Call your doctor for medical advice about side effects. You may report side effects to FDA at 1-800-FDA-1088.
You may also report side effects to VIVUS LLC at 1-888-998-4887.

How should I store PANCREAZE?

- Store PANCREAZE at room temperature between 59°F and 77°F (15°C and 25°C). Avoid heat.
- Keep PANCREAZE in a dry place and in the original container.
- After opening the bottle, keep it tightly closed between uses.
- All PANCREAZE bottles contain a desiccant canister. Do not eat or throw away the desiccant canister in your medicine bottle. This canister will protect your medicine from moisture.

Keep PANCREAZE and all medicines out of the reach of children.

General information about PANCREAZE
Medicines are sometimes prescribed for purposes other than those listed in a Medication Guide. Do not use PANCREAZE for a condition for which it was not prescribed. Do not give PANCREAZE to other people, even if they have the same symptoms you have. It may harm them.
You can ask your pharmacist or doctor for information about PANCREAZE that is written for healthcare professionals.

What are the ingredients in PANCREAZE?
Active Ingredient: lipase, protease, amylase
Inactive ingredients in all strengths of PANCREAZE: colloidal silicon dioxide, crospovidone, magnesium stearate, methacrylic acid ethyl acrylate copolymer, microcrystalline cellulose, montan glycol wax, simethicone emulsion, talc and triethyl citrate. The capsule shell contains hypromellose, titanium dioxide and iron oxide.
Imprint ink for PANCREAZE 2600 contains black iron oxide, shellac, propylene glycol, strong ammonia solution, potassium hydroxide.
Imprint ink for PANCREAZE 4200, 10500 and 16800 contains black iron oxide, shellac-glaze-45%, ammonium hydroxide, propylene glycol.
Imprint ink for PANCREAZE 21000 contains yellow iron oxide, shellac, strong ammonia solution, propylene glycol.
Imprint ink for PANCREAZE 37000 contains black iron oxide, shellac-glaze-45%, ammonium hydroxide, propylene glycol.
For more information go to www.pancreaze.net or call 1-888-998-4887.
Product of Germany
Finished Product Manufactured at:
Nordmark Pharma GmbH
25436 Uetersen, Germany.
Manufactured by:
VIVUS LLC
900 E. Hamilton Ave., Suite 550
Campbell, CA 95008, USA

This Medication Guide has been approved by the U.S. Food and Drug Administration.

2/2024

©VIVUS LLC 2010-2024
U.S. License No. 2197
PH-10-001-07

PRINCIPAL DISPLAY PANEL - 100 Capsule Bottle Carton - NDC 62541-402-10

NDC 62541-402-10

pancrelipase
PANCREAZE®
Delayed-Release Capsules

Each capsule contains:

Lipase 4,200 USP Units
Amylase 24,600 USP Units
Protease 14,200 USP Units

DOSE BY LIPASE UNITS

Each delayed-release capsule
contains enteric coated pancrelipase
microtablets.
This product is of porcine origin.

Attention Pharmacist:
Dispense the accompanying
Medication Guide to each patient.

Rx only.

100
delayed-release
capsules

PRINCIPAL DISPLAY PANEL - 100 Capsule Bottle Carton - NDC 62541-403-10

NDC 62541-403-10

pancrelipase
PANCREAZE®
Delayed-Release Capsules

Each capsule contains:

Lipase 10,500 USP Units
Amylase 61,500 USP Units
Protease 35,500 USP Units

DOSE BY LIPASE UNITS

Each delayed-release capsule contains
enteric coated pancrelipase microtablets.
This product is of porcine origin.

Attention Pharmacist:
Dispense the accompanying
Medication Guide to each patient.

Rx only.

100
delayed-release
capsules

PRINCIPAL DISPLAY PANEL - 100 Capsule Bottle Carton - NDC 62541-404-10

NDC 62541-404-10

pancrelipase
PANCREAZE®
Delayed-Release Capsules

Each capsule contains:

Lipase 16,800 USP Units
Amylase 98,400 USP Units
Protease 56,800 USP Units

DOSE BY LIPASE UNITS

Each delayed-release capsule contains
enteric coated pancrelipase microtablets.
This product is of porcine origin.

Attention Pharmacist:
Dispense the accompanying
Medication Guide to each patient.

Rx only.

100
delayed-release
capsules

PRINCIPAL DISPLAY PANEL - 100 Capsule Bottle Carton - NDC 62541-405-10

NDC 62541-405-10

pancrelipase
PANCREAZE®
Delayed-Release Capsules

Each capsule contains:

Lipase 21,000 USP Units
Amylase 83,900 USP Units
Protease 54,700 USP Units

DOSE BY LIPASE UNITS

Each delayed-release capsule contains
enteric coated pancrelipase microtablets.
This product is of porcine origin.

Attention Pharmacist:
Dispense the accompanying
Medication Guide to each patient.

Rx only.

100
delayed-release
capsules

PRINCIPAL DISPLAY PANEL - 100 Capsule Bottle Carton - NDC 62541-401-10

NDC 62541-401-10

pancrelipase
PANCREAZE
Delayed-Release Capsules

Each capsule contains:

Lipase 2,600 USP Units
Amylase 15,200 USP Units
Protease 8,800 USP Units

DOSE BY LIPASE UNITS

Each delayed-release capsule
contains enteric coated pancrelipase
microtablets.
This product is of porcine origin.

Attention Pharmacist:
Dispense the accompanying
Medication Guide to each patient.

Rx only.

100
delayed-release
capsules

PRINCIPAL DISPLAY PANEL - 100 Capsule Bottle Carton - NDC 62541-406-10

NDC 62541-406-10
Contains 2 bottles of 50 delayed-release capsules in a carton

pancrelipase
PANCREAZE®
Delayed-Release Capsules

Each capsule contains:

Lipase 37,000 USP Units
Amylase 149,900 USP Units
Protease 97,300 USP Units

DOSE BY LIPASE UNITS

Each delayed-release capsule contains enteric coated
pancrelipase microtablets.
This product is of porcine origin.

Attention Pharmacist:
Dispense the accompanying Medication Guide to each patient.

Rx only.

100
delayed-release
capsules